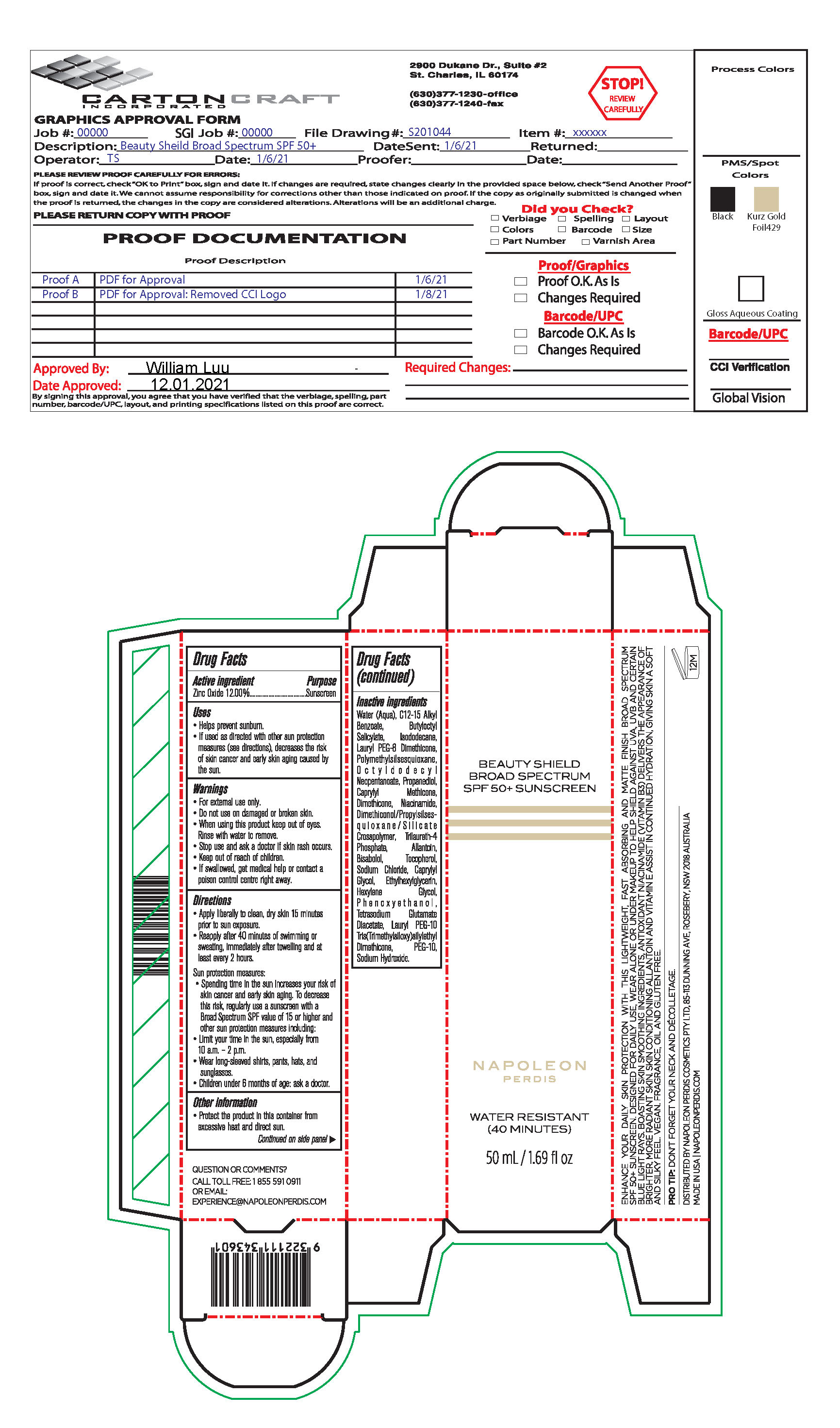 DRUG LABEL: BEAUTY SHIELD BROAD SPECTRUM SUNSCREEN (Napoleon Perdis)
NDC: 51386-291 | Form: LOTION
Manufacturer: Napoleon PerdisCosmetic Pty Ltd
Category: otc | Type: HUMAN OTC DRUG LABEL
Date: 20251009

ACTIVE INGREDIENTS: ZINC OXIDE 132 mg/1 mL
INACTIVE INGREDIENTS: POLYSORBATE 20; SODIUM HYDROXIDE; WATER; NIACINAMIDE; ETHYLHEXYLGLYCERIN; HEXYLENE GLYCOL; GLYCERIN; DIMETHICONOL/PROPYLSILSESQUIOXANE/SILICATE CROSSPOLYMER (450000000 MW); PROPANEDIOL; TETRASODIUM GLUTAMATE DIACETATE; CARRAGEENAN; SODIUM CHLORIDE; PHENOXYETHANOL; PALMITOYL TRIPEPTIDE-1; .BETA.-TOCOPHEROL; POLYMETHYLSILSESQUIOXANE (4.5 MICRONS); PALMITOYL TETRAPEPTIDE-7; TRILAURETH-4 PHOSPHATE; BUTYLOCTYL SALICYLATE; OCTYLDODECYL NEOPENTANOATE; ISODODECANE; .ALPHA.-BISABOLOL, (+)-; BUTYLENE GLYCOL

BEAUTY SHIELD BROAD SPECTRUM SUNSCREEN (Napoleon Perdis)